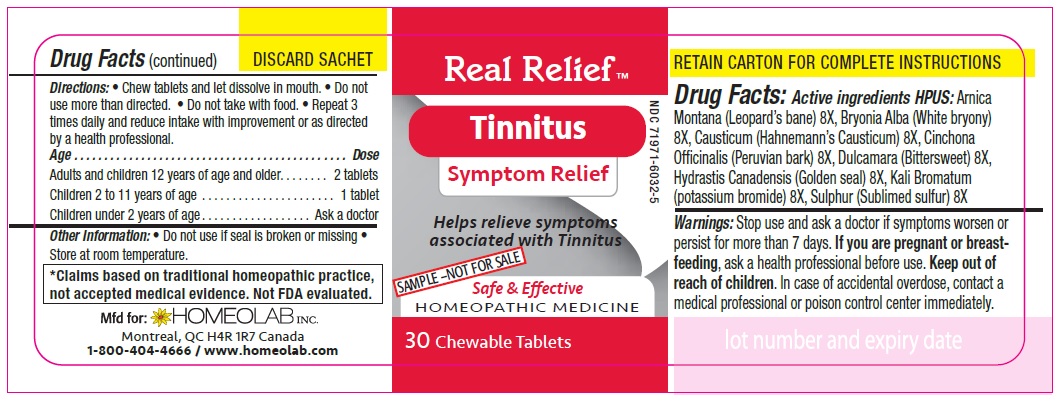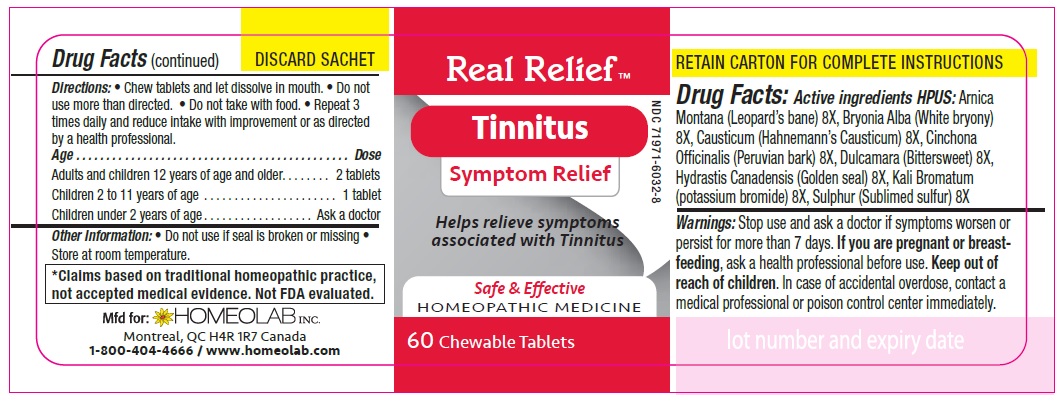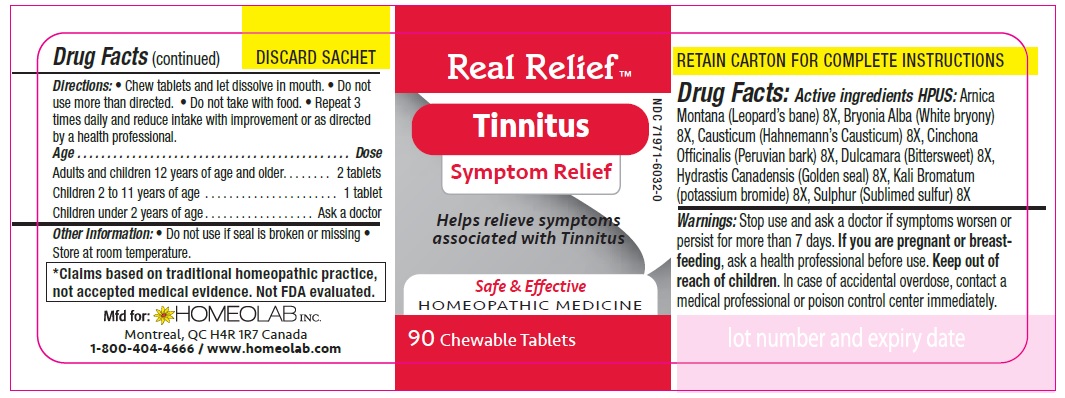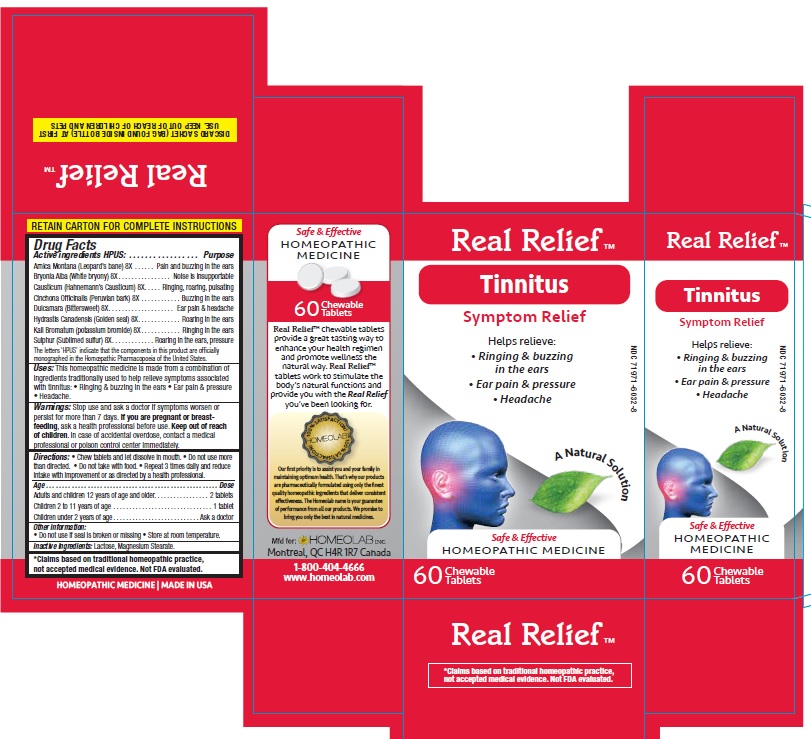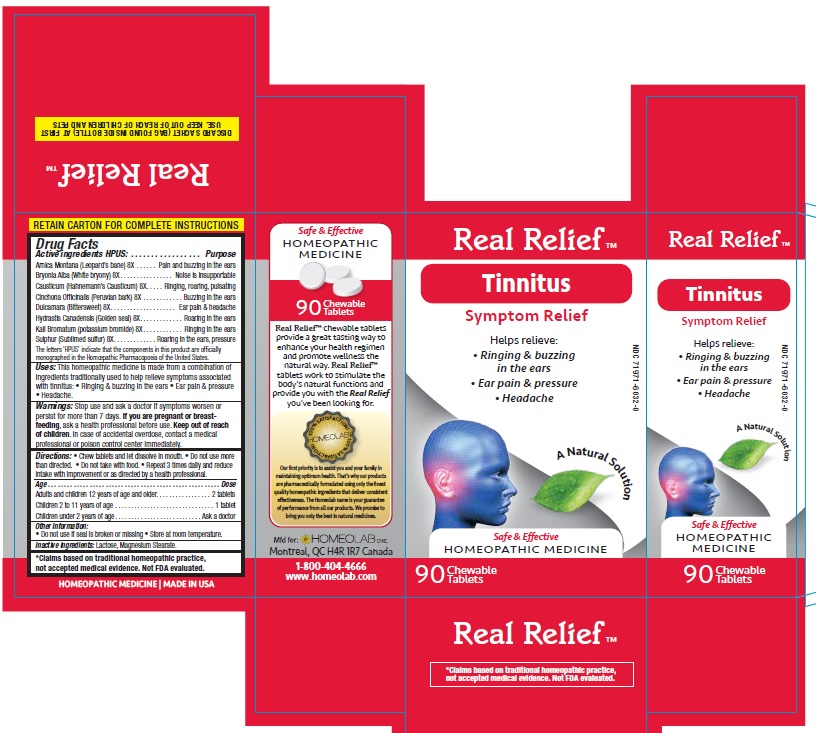 DRUG LABEL: Real Relief
NDC: 65808-326 | Form: TABLET
Manufacturer: GMP Laboratories of America, Inc.
Category: homeopathic | Type: HUMAN OTC DRUG LABEL
Date: 20201229

ACTIVE INGREDIENTS: ARNICA MONTANA 8 [hp_X]/1 1; BRYONIA ALBA ROOT 8 [hp_X]/1 1; CAUSTICUM 8 [hp_X]/1 1; CINCHONA OFFICINALIS BARK 8 [hp_X]/1 1; SOLANUM DULCAMARA TOP 8 [hp_X]/1 1; GOLDENSEAL 8 [hp_X]/1 1; POTASSIUM BROMIDE 8 [hp_X]/1 1; SULFUR 8 [hp_X]/1 1
INACTIVE INGREDIENTS: LACTOSE MONOHYDRATE; MAGNESIUM STEARATE

Active Ingredients HPUS:

Arnica montana (Leopard's bane) 8[hp-X]

Bryonia (White bryony) 8 [hp-X]

Causticum (Hahnmann's causticum) 8 [hp-X]

Cinchona officinalis (Peruvian bark) 8 [hp-X]

Dulcamara (Bittersweet) 8 [hp-X]

Hydrastis canadensis (Golden seal) 8 [hp-X]

Kali bromatum (Potassium bromide) 8 [hp-X]

Sulphur (Sublimed sulfur) 8 [hp-X]

Purpose

Homeopathic remedy helps relieve symptoms of tinnitus:

- Rigging and buzzing in the ears
- Ear pain & pressure
- Headache

The letters 'HPUS' indicate that the components in this product are officially monographed in the Homoeopathic Pharmacopoeia of the United States.

*Claims based on traditional homeopathic practice, not accepted medical evidence. Not FDA evaluated.

Uses

This homeopathic medicine is made from a combination of ingredients traditionally used to help relieve symptoms associated

- with tinnitus
- Rigging and buzzing in the ears
- Ear pain & pressure
- Headache

Warnings

Stop use and ask a doctor if symptoms worsen or last for more than 7 days.

If you are pregnant or breastfeeding, ask a health professional before use.

Keep out of reach of children.

In case of accidental overdose, contact a medical professional or poison control center immediately.

Directions

Chew tablets and let dissolve in mouth.

Do not use more than directed.

Do not take with food.

Repeat 3 times daily and reduce intake with improvement or as directed by a health professional

Age…………………………………………………………........ Dose

Adults and Children 12 years of age and older………...... 2 tablets

Children 2 to 11 years of age…...……………………............ 1 tablet

Children under 2 years of age……………………................. Ask a doctor

Other information

- Store at room temperature.
- Do not use if seal is broken or missing.

Inactive ingredients

Lactose, Magnesium Stearate.